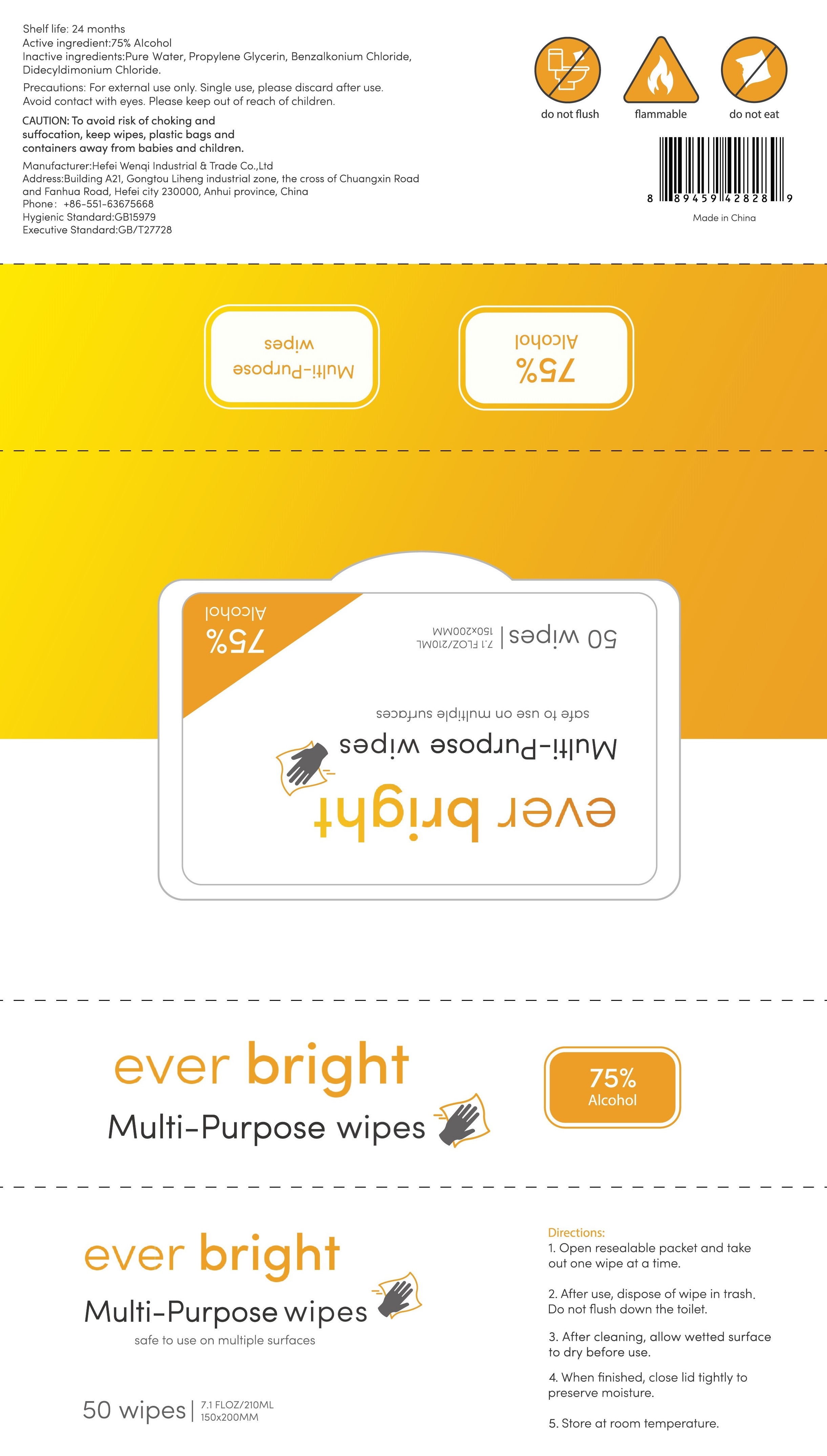 DRUG LABEL: Multi-purpose wipes
NDC: 76991-005 | Form: CLOTH
Manufacturer: Hefei Wenqi Industrial & Trade Co., Ltd
Category: otc | Type: HUMAN OTC DRUG LABEL
Date: 20200718

ACTIVE INGREDIENTS: ALCOHOL 75 1/100 1
INACTIVE INGREDIENTS: BENZALKONIUM CHLORIDE; DIDECYLDIMONIUM CHLORIDE; PROPYLENE GLYCOL; WATER

Multi-purpose wipes

Active Ingredient(s)

75% Alcohol

Purpose

/

Use

To avoid risk of choking and Sffocation, keep wipes, plastic bags and containers away from babies and children

Warnings

For external use only. Single use, please discard after use.
Avoid contact with eyes.

Do not use

/

WHEN USING

/

STOP USE

/

Please keep out of reach of children

Directions

1. Open resealable packet and takeout one wipe at a time
2. After use, dispose of wipe in trashDo not flush down the toilet
3. After cleaning, allow wetted surfaceto dry before use
4. When finished, close lid tightly topreserve moisture
5. Store at room temperature

Other information

/

Inactive ingredients

Pure Water, Propylene Glycerin, Benzalkonium Chloride,Didecyldimonium Chloride